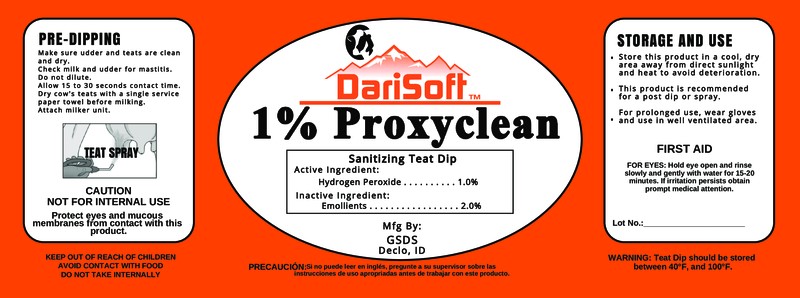 DRUG LABEL: Proxyclean
NDC: 86186-101 | Form: SOLUTION
Manufacturer: Gem State Dairy Supply
Category: animal | Type: OTC ANIMAL DRUG LABEL
Date: 20230619

ACTIVE INGREDIENTS: HYDROGEN PEROXIDE 10 g/1 L

1% Proxyclean

Active Ingredient:

Hydrogen Peroxide............................ 1.0%

INDICATIONS AND USAGE

Sanitizing Teat Dip

Teat Spray

PRE-DIPPING

Make sure udder and teats are clean and dry.

Check milk and udder for mastitis.

Do not dilute.

Allow 15 to 30 seconds contact time.

Dry cow's teats with a single service paper towel before milking.

Attach milker unit.

WARNINGS

CAUTION

NOT FOR INTERNAL USE

Protect eyes and mucous membranes from contact with this product.

Avoid contact with food

Do not take internally

STORAGE AND USE

- Store this product in a cool, dry area away from direct sunlight and heat to avoid deterioration.
- This product is recommended for a post dip or spray.
- For prolonged use, wear gloves and use in a well ventilated area.

WARNING: Teat dip should be stored between 40°F and 100°F.

FIRST AID

FOR EYES: Hold eye open and rinse slowly and gently with water for 15-20 minutes. If irritation persists, optain prompt medical attention.

KEEP OUT OF REACH OF CHILDREN

Inactive Ingredient:

Emollients.................................2.0%

PACKAGE LABEL

Add image transcription here...